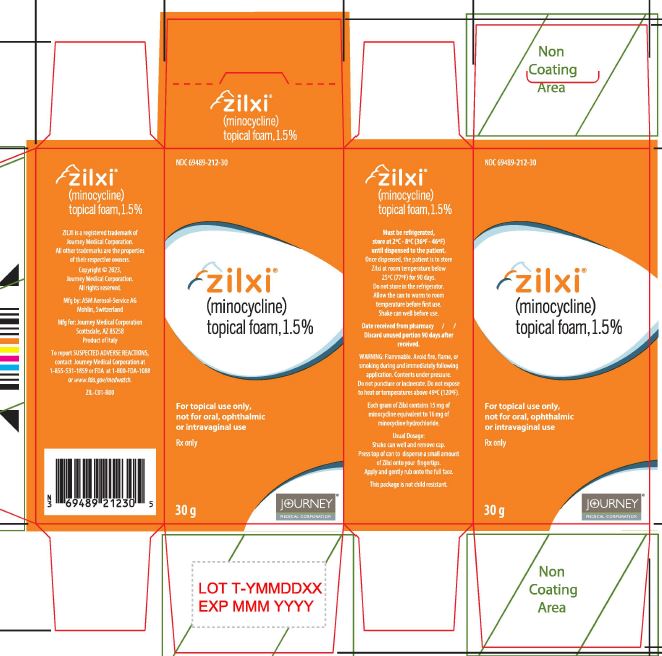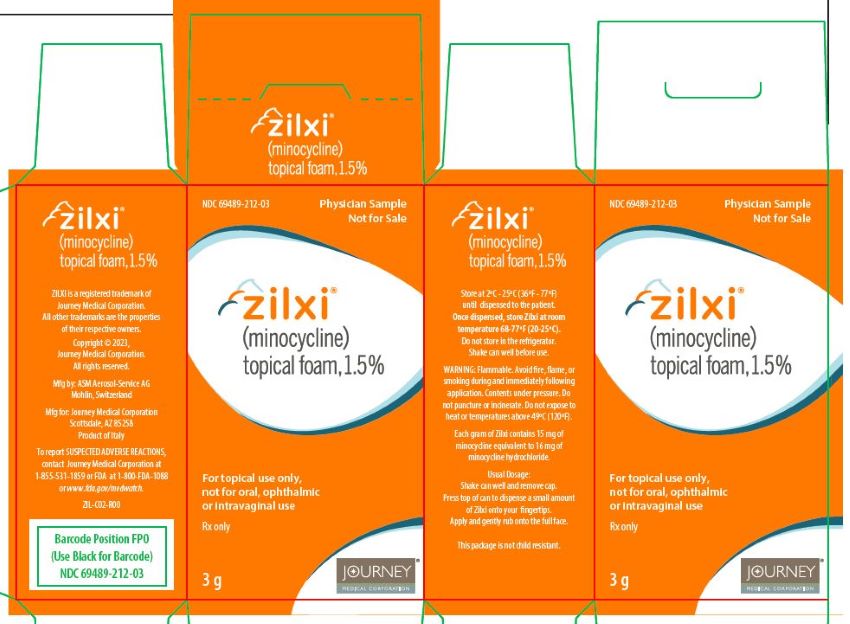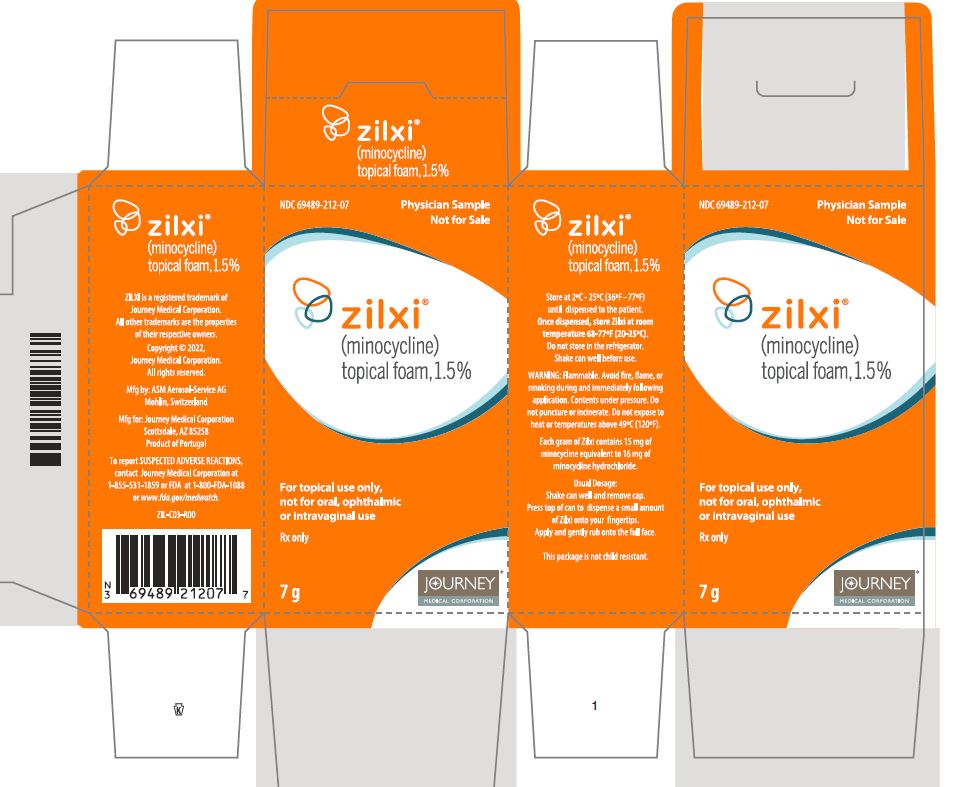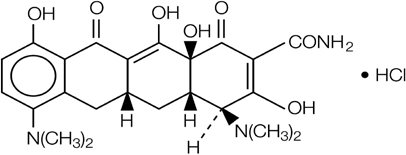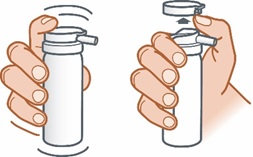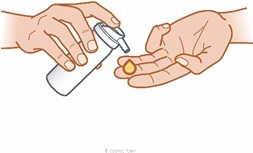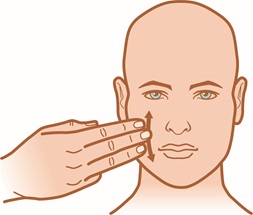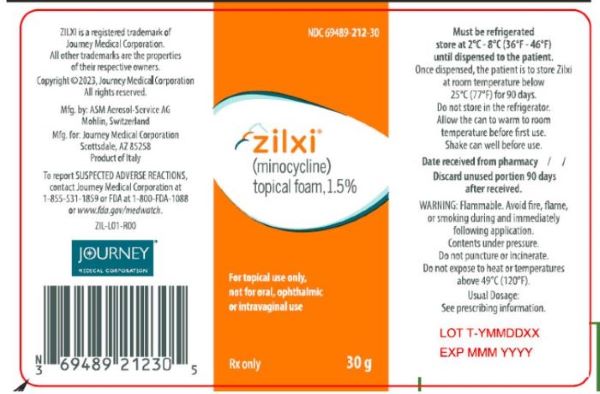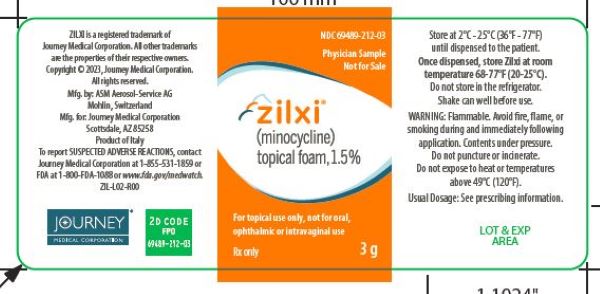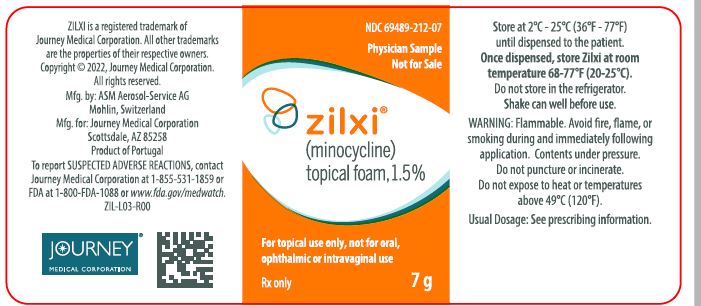 DRUG LABEL: ZILXI
NDC: 69489-212 | Form: AEROSOL, FOAM
Manufacturer: Journey Medical Corporation
Category: prescription | Type: HUMAN PRESCRIPTION DRUG LABEL
Date: 20240209

ACTIVE INGREDIENTS: MINOCYCLINE HYDROCHLORIDE 15 mg/1 g
INACTIVE INGREDIENTS: SOYBEAN OIL; COCONUT OIL; LIGHT MINERAL OIL; CYCLOMETHICONE; CETOSTEARYL ALCOHOL; STEARIC ACID; MYRISTYL ALCOHOL; HYDROGENATED CASTOR OIL; WHITE WAX; STEARYL ALCOHOL; DOCOSANOL; BUTANE; ISOBUTANE; PROPANE

HIGHLIGHTS OF PRESCRIBING INFORMATION

These highlights do not include all the information needed to use ZILXI safely and effectively. See full prescribing information for ZILXI.
ZILXI® (minocycline) topical foam
Initial U.S. Approval: 1971

1 INDICATIONS AND USAGE

ZILXI is a tetracycline-class drug indicated for the treatment of inflammatory lesions of rosacea in adults. (1)
Limitations of Use

This formulation of minocycline has not been evaluated in the treatment of infections. To reduce the development of drug-resistant bacteria as well as to maintain the effectiveness of other antibacterial drugs, ZILXI should be used only as indicated (1).

2 DOSAGE AND ADMINISTRATION

Apply ZILXI over all areas of the face once daily. ZILXI should be gently rubbed into the skin. (2)

3 DOSAGE FORMS AND STRENGTHS

Foam, 1.5%. (3)

4 CONTRAINDICATIONS

This drug is contraindicated in persons who have shown hypersensitivity to any of the tetracyclines or any of the ingredients in ZILXI. (4)

5 WARNINGS AND PRECAUTIONS

- The propellant in ZILXI is flammable. Instruct the patient to avoid fire, flame, and smoking during and immediately following application. (5.1)
- The use of tetracycline-class of drugs orally during the second and third trimesters of pregnancy, infancy and childhood up to the age of 8 years may cause permanent discoloration of the teeth (yellow-gray-brown) and reversible inhibition of bone growth. (5.2, 5.3, 5.4, 8.4)
- If Clostridioides difficile associated diarrhea occurs, discontinue ZILXI. (5.5)
- If liver injury is suspected, discontinue ZILXI. (5.6)
- If renal impairment exists, oral minocycline doses may need to be adjusted to avoid excessive systemic accumulations of the drug and possible liver toxicity. (5.7)
- Oral minocycline may cause central nervous system side effects including lightheadedness, dizziness, or vertigo. (5.8)
- Oral minocycline may cause intracranial hypertension in adults and adolescents. Discontinue ZILXI if symptoms occur. (5.9)
- Oral minocycline has been associated with autoimmune syndromes; discontinue ZILXI immediately if symptoms occur. (5.10)
- Photosensitivity can occur with oral tetracycline. Patients should minimize or avoid exposure to natural or artificial sunlight. (5.11)
- Oral minocycline has been associated with anaphylaxis, serious skin reactions, erythema multiforme, and DRESS syndrome. Discontinue ZILXI immediately if symptoms occur. (5.12)

6 ADVERSE REACTIONS

The most commonly observed adverse reaction (incidence ≥1%) is diarrhea. (6.1)

To report SUSPECTED ADVERSE REACTIONS, contact Journey Medical Corporation at 1-855-531-1859 or FDA at 1-800-FDA-1088 or www.fda.gov/medwatch.

7 DRUG INTERACTIONS

- Patients on anticoagulant therapy may require downward adjustment of their anticoagulant dosage. (7.1)
- Penicillin: avoid coadministration. (7.2)

8 USE IN SPECIFIC POPULATIONS

- Minocycline like other tetracycline-class drugs can cause fetal harm when administered orally to a pregnant woman. (5.2, 5.3, 5.4, 8.1)
- The use of drugs of the tetracycline-class orally during tooth development may cause permanent discoloration of teeth. (5.3, 8.1, 8.2, 8.4)
- Lactation: Breastfeeding not recommended. (8.2)

FULL PRESCRIBING INFORMATION

1 INDICATIONS AND USAGE

ZILXI is indicated for the treatment of inflammatory lesions of rosacea in adults [see Clinical Studies (14)].

Limitations of Use

This formulation of minocycline has not been evaluated in the treatment of infections. To reduce the development of drug-resistant bacteria as well as to maintain the effectiveness of other antibacterial drugs, ZILXI should be used only as indicated [see Warnings and Precautions (5.14)].

2 DOSAGE AND ADMINISTRATION

For topical use only, not for oral, ophthalmic or intravaginal use.

After shaking the can well, a small amount of topical foam (e.g. a cherry-sized amount) should be expressed from the can onto the fingertips of the hand and then applied as a thin layer over all areas of the face. Additional ZILXI foam may be used as needed to ensure the entire face is treated. The topical foam should be applied at approximately the same time each day at least 1 hour before bedtime. The patient should not bathe, shower or swim for at least 1 hour after application of the product.

3 DOSAGE FORMS AND STRENGTHS

Topical foam, 1.5%.

Each gram of ZILXI contains 15 mg of minocycline equivalent to 16 mg of minocycline hydrochloride and is supplied as a yellow suspension in a pressurized aluminum aerosol container (can).

4 CONTRAINDICATIONS

This drug is contraindicated in persons who have shown hypersensitivity to any of the tetracyclines or any other ingredients in ZILXI.

5 WARNINGS AND PRECAUTIONS

5.1 Flammability

The propellant in ZILXI is flammable. Instruct the patient to avoid fire, flame, and smoking during and immediately following application. Do not puncture and/or incinerate the containers. Do not expose containers to heat and/or store at temperatures above 120°F (49°C).

5.2 Teratogenic Effects

Minocycline, like other tetracycline-class drugs, may inhibit bone growth when administered orally during pregnancy. Based on animal data, when administered orally, tetracyclines cross the placenta, are found in fetal tissues, and can cause skeletal malformation and retardation of skeletal development on the developing fetus [see Use in Specific Populations (8.1) and Nonclinical Toxicology (13.1)].

5.3 Tooth Discoloration

The use of tetracycline class drugs orally during tooth development (second and third trimesters of pregnancy, infancy, and childhood up to the age of 8 years) may cause permanent discoloration of the teeth (yellow-gray-brown). This adverse reaction is more common during long-term oral use of the tetracycline but has been observed following repeated short-term courses. Enamel hypoplasia has also been reported with oral tetracycline drugs. Use of tetracycline drugs is not recommended during tooth development.

5.4 Inhibition of Bone Growth

All tetracyclines form a stable calcium complex in any bone-forming tissue. A decrease in fibula growth rate has been observed in premature human infants given oral tetracycline in doses of 25 mg/kg every 6 hours. This reaction was shown to be reversible when the drug was discontinued.

Results of animal studies indicate that oral tetracyclines cross the placenta, are found in fetal tissues, and can cause retardation of skeletal development on the developing fetus. Evidence of embryotoxicity has been noted in animals treated orally early in pregnancy [see Use in Specific Populations (8.1)].

5.5 Clostridioides difficile Associated Diarrhea

Clostridioides difficile associated diarrhea (CDAD) has been reported with nearly all antibacterial agents, including oral minocycline, and may range in severity from mild diarrhea to fatal colitis. Treatment with antibacterial agents alters the normal flora of the colon leading to overgrowth of C. difficile.

C. difficile produces toxins A and B which contribute to the development of CDAD. Hypertoxin producing strains of C. difficile cause increased morbidity and mortality, as these infections can be refractory to antimicrobial therapy and may require colectomy. CDAD must be considered in all patients who present with diarrhea following antibiotic use. Careful medical history is necessary since CDAD has been reported to occur over two months after the administration of antibacterial agents.

If CDAD is suspected or confirmed, antibiotic use not directed against C. difficile may need to be discontinued. Appropriate fluid and electrolyte management, protein supplementation, antibiotic treatment of C. difficile, and surgical evaluation should be instituted as clinically indicated.

5.6 Hepatotoxicity

Post-marketing cases of serious liver injury, including irreversible drug-induced hepatitis and fulminant hepatic failure (sometimes fatal) have been reported with oral minocycline use.

5.7 Metabolic Effects

The anti-anabolic action of the tetracyclines may cause an increase in blood urea nitrogen (BUN). In patients with significantly impaired function, higher serum levels of tetracycline-class drugs may lead to azotemia, hyperphosphatemia, and acidosis. If renal impairment exists, recommended oral or parenteral doses may lead to excessive systemic accumulations of the drug and possible liver toxicity. Under such conditions, adjust the dose downward, and if therapy is prolonged, serum level determinations of the drug may be advisable.

5.8 Central Nervous System Effects

Central nervous system side effects including light-headedness, dizziness or vertigo have been reported with oral minocycline therapy. Patients who experience these symptoms should be cautioned about driving vehicles or using hazardous machinery while on minocycline therapy. These symptoms may disappear during therapy and may disappear when the drug is discontinued.

5.9 Intracranial Hypertension

Intracranial hypertension has been associated with the use of oral tetracycline-class drugs. Clinical manifestations of intracranial hypertension include headache, blurred vision, diplopia and vision loss; papilledema can be found on fundoscopy. Women of childbearing age who are overweight or have a history of IH are at a greater risk for developing intracranial hypertension. Patients should be questioned for visual disturbances prior to initiation of treatment with tetracyclines. Concomitant use of isotretinoin and tetracycline should be avoided because isotretinoin, a systemic retinoid, is also known to cause intracranial hypertension.

Although intracranial hypertension typically resolves after discontinuation of treatment, the possibility for permanent visual loss exists. If visual disturbance occurs during treatment, prompt ophthalmologic evaluation is warranted. Because intracranial pressure can remain elevated for weeks after drug cessation, patients should be monitored until they stabilize.

5.10 Autoimmune Syndromes

Tetracyclines have been associated with the development of autoimmune syndromes. The long-term use of oral minocycline has been associated with drug-induced lupus-like syndrome, autoimmune hepatitis and vasculitis. Sporadic cases of serum sickness have presented shortly after oral minocycline use. Symptoms may be manifested by fever, rash, arthralgia, and malaise. In symptomatic patients, immediately discontinue the use of all tetracycline-class drugs, including ZILXI.

5.11 Photosensitivity

Photosensitivity manifested by an exaggerated sunburn reaction has been observed in some individuals taking oral tetracyclines; this reaction has been reported less frequently with minocycline. Although ZILXI did not induce phototoxicity or photoallergic responses in human dermal safety studies, patients should minimize or avoid exposure to natural or artificial sunlight (tanning beds or UVA/B treatment) while using minocycline. If patients need to be outdoors while using ZILXI, they should wear loose-fitting clothes that protect skin from sun exposure and discuss other sun protection measures with their physician. Advise patients to discontinue treatment with ZILXI at the first evidence of sunburn.

5.12 Serious Skin/Hypersensitivity Reaction

Cases of anaphylaxis, serious skin reactions (e.g. Stevens Johnson syndrome), erythema multiforme, and drug reaction with eosinophilia and systemic symptoms (DRESS) syndrome have been reported postmarketing with oral minocycline use. DRESS syndrome consists of cutaneous reaction (such as rash or exfoliative dermatitis), eosinophilia, and one or more of the following visceral complications such as: hepatitis, pneumonitis, nephritis, myocarditis, and pericarditis. Fever and lymphadenopathy may be present. In some cases, death has been reported with oral minocycline use. If this syndrome is recognized, discontinue ZILXI immediately.

5.13 Tissue Hyperpigmentation

Oral tetracyclines are known to cause hyperpigmentation. Tetracycline therapy may induce hyperpigmentation in many organs, including nails, bone, skin, eyes, thyroid, visceral tissue, oral cavity (teeth, mucosa, alveolar bone), sclerae and heart valves. Skin and oral pigmentation has been reported to occur independently of time or amount of drug administration, whereas other tissue pigmentation has been reported to occur upon prolonged administration. Skin pigmentation includes diffuse pigmentation as well as pigmentation over sites of scars or injury.

5.14 Development of Drug-Resistant Bacteria

ZILXI has not been evaluated in the treatment of infections. Bacterial resistance to the tetracyclines may develop in patients using ZILXI, therefore, the susceptibility of bacteria associated with infection should be considered in selecting antimicrobial therapy. Because of the potential for drug-resistant bacteria to develop during the use of ZILXI, it should be used only as indicated.

5.15 Superinfection/Potential for Microbial Overgrowth

Use of ZILXI may result in overgrowth of non-susceptible organisms, including fungi. If superinfection occurs, discontinue ZILXI and institute appropriate therapy.

6 ADVERSE REACTIONS

6.1 Clinical Trials Experience

Because clinical trials are conducted under widely varying conditions, adverse reaction rates observed in the clinical trials of a drug cannot be directly compared to rates in the clinical trials of another drug and may not reflect the rates observed in practice.

In three (two Phase 3 and one Phase 2) multicenter, randomized, double-blind, vehicle-controlled trials, adult subjects applied ZILXI or vehicle once daily for 12 weeks. A total of 1,087 subjects were treated with ZILXI and 591 with vehicle. The majority of subjects were White (97%) and female (70%). Approximately 67% were non-Hispanic/Latino. The mean age was 50.0 years and ages ranged from 18 to 86 years.

The most common adverse reaction reported by ≥1% of subjects treated with ZILXI and more frequently than in subjects treated with vehicle was diarrhea (1% vs. 0%), respectively.

During the two Phase 3 trials, local tolerability evaluations were conducted at each study visit by assessment of erythema, telangiectasia, burning/stinging, flushing/blushing, dryness, itching, peeling and hyperpigmentation. Table 1 presents local tolerance assessments by incidence rate (%) and severity grade.

Subjects treated with ZILXI had improved local tolerability signs and symptoms at Week 12 when compared with corresponding baseline values. These occurred at a similar frequency and severity as subjects treated with the vehicle component of ZILXI.

Table 1: Facial Cutaneous Tolerability Assessment
 | ZILXI, (%); (N=1,008**)
Symptom/Severity | Mild | Moderate | Severe
Erythema | 36.2 | 18.3 | 0.7
Telangiectasia | 61.0 | 18.8 | 0
Burning/Stinging | 13.3 | 2.8 | 0
Flushing/Blushing | 39.0 | 9.6 | 0.9
Dryness | 23.9 | 4.0 | 0.1
Itching | 20.0 | 3.3 | 0
Skin Peeling | 16.1 | 1.9 | 0.1
Hyperpigmentation* | 22.5 | 2.8 | 0
*Hyperpigmentation was most frequently assessed as characteristic of inflammatory and post-inflammatory changes associated with inflammatory lesions of rosacea.
** Of 1,008 subjects, 897 had local tolerability assessments at Week 12.

In a 40-week open-label extension safety study of ZILXI (for a total of up to 52 weeks of treatment) [NCT03276936], frequency and severity of local tolerability signs and symptoms at Week 52 were comparable to those reported at Week 12.

7 DRUG INTERACTIONS

7.1 Anticoagulants

Because tetracyclines have been shown to depress plasma prothrombin activity, patients who are on anticoagulant therapy may require downward adjustment of their anticoagulant dosage.

7.2 Penicillin

Since bacteriostatic drugs may interfere with the bactericidal action of penicillin, it is advisable to avoid giving tetracycline-class drugs in conjunction with penicillin.

7.3 Drug/Laboratory Test Interactions

False elevations of urinary catecholamine levels may occur due to interference with the fluorescence test.

8 USE IN SPECIFIC POPULATIONS

8.1 Pregnancy

Risk Summary

Available data with ZILXI use in pregnant women are insufficient to evaluate for a drug-associated risk of major birth defects, miscarriage or other adverse maternal or fetal outcomes. Systemic absorption of ZILXI in humans is low following once daily topical administration of ZILXI under maximal clinical use conditions [see Clinical Pharmacology (12.3)]. Because of low systemic exposure, it is not expected that maternal use of ZILXI will result in significant fetal exposure to the drug.

Tetracycline-class drugs may cause permanent discoloration of teeth and reversible inhibition of bone growth when administered orally during pregnancy [see Warnings and Precautions 5.2, 5.3, 5.4).

Animal reproduction studies were not conducted with ZILXI. In animal reproduction studies, oral administration of minocycline to pregnant rats and rabbits during organogenesis induced skeletal malformations in fetuses at systemic exposures of 2,000 and 1,300 times, respectively, the maximum recommended human dose (MRHD based on AUC comparison) of ZILXI (see Data).

The estimated background risk of major birth defects and miscarriage for the indicated population is unknown. All pregnancies have a background risk of birth defect, loss, or other adverse outcomes. In the U.S. general population, the estimated background risk of major birth defects and miscarriage in clinically recognized pregnancies is 2-4% and 15-20%, respectively.

Data

Animal Data

Results of animal studies with oral administration indicate that tetracyclines cross the placenta, are found in fetal tissues, and can cause retardation of skeletal development of the developing fetus.

Minocycline induced skeletal malformations (bent limb bones) in fetuses when orally administered to pregnant rats and rabbits during the period of organogenesis at doses of 30 mg/kg/day and 100 mg/kg/day, respectively, (2,000 times and 1,300 times, respectively, the systemic exposure at the MRHD based on AUC comparison). Reduced mean fetal body weight was observed when minocycline was orally administered to pregnant rats during the period of organogenesis at a dose of 10 mg/kg/day (680 times the systemic exposure at the MRHD based on AUC comparison).

Minocycline was assessed for effects on peri- and post-natal development of rats in a study that involved oral administration to pregnant rats during the period of organogenesis through lactation, at doses of 5, 10, or 50 mg/kg/day. In this study, body weight gain was significantly reduced in pregnant females that received 50 mg/kg/day (1,700 times the systemic exposure at the MRHD based on AUC comparison). No effects of treatment on the duration of the gestation period or the number of live pups born per litter were observed. Gross external anomalies observed in F1 pups (offspring of animals that received minocycline) included reduced body size, improperly rotated forelimbs, and reduced size of extremities. No effects were observed on the physical development, behavior, learning ability, or reproduction of F1 pups, and there was no effect on gross appearance of F2 pups (offspring of F1 animals).

8.2 Lactation

Risk Summary

Tetracycline-class drugs, including minocycline, are present in breast milk following oral administration. It is not known whether minocycline is present in human milk after topical administration to the nursing mother. There are no data on the effects of minocycline on milk production. Because of the potential for serious adverse reactions, advise patients that breastfeeding is not recommended during treatment with ZILXI [see Warnings and Precautions (5.2)].

8.4 Pediatric Use

The safety and effectiveness of ZILXI for the treatment of inflammatory lesions of rosacea have not been evaluated in pediatric patients.

8.5 Geriatric Use

There were 278 subjects aged 65 or older in the clinical trials of ZILXI (16.6% of 1,678 subjects). No overall differences in safety or effectiveness were observed between these subjects and younger subjects, and other reported clinical experience has not identified differences in responses between the elderly and younger patients, but greater sensitivity of some older individuals cannot be ruled out.

11 DESCRIPTION

Minocycline hydrochloride, a semi-synthetic derivative of tetracycline, is [4S‑(4α,4aα,5aα,12aα)]-4,7-bis(dimethylamino)-1,4,4a,5,5a,6,11,12a-octahydro-3,10,12,12a‑tetrahydroxy-1,11-dioxo-2-naphthacenecarboxamide monohydrochloride. The structural formula is represented below:

C23 H27 N3 O7•HClM. W. 493.94

Each gram of ZILXI contains micronized 15 mg minocycline equivalent to 16 mg minocycline hydrochloride in a yellow suspension foam.

In addition, the 1.5% ZILXI topical foam contains the following inactive ingredients: soybean oil, coconut oil, light mineral oil, cyclomethicone, cetostearyl alcohol, stearic acid, myristyl alcohol, hydrogenated castor oil, white wax (beeswax), stearyl alcohol, docosanol. ZILXI topical foam is dispensed from an aluminum container (can) pressurized with propellant (butane + isobutane + propane).

12 CLINICAL PHARMACOLOGY

12.1 Mechanism of Action

The mechanism of action of ZILXI for the treatment of inflammatory lesions of rosacea is unknown.

12.2 Pharmacodynamics

The pharmacodynamics of ZILXI for the treatment of inflammatory lesions of rosacea are unknown.

12.3 Pharmacokinetics

In a pharmacokinetic study, male and female subjects 18 years of age or older with inflammatory lesions of rosacea (N=20) applied approximately 2 grams of ZILXI topically to the face once daily for 14 days.

The mean ± SD maximum plasma concentration (Cmax) and area under the concentration time curve from 0 to 24 hours post dose (AUC0-24h) for minocycline on Day 1 were 1.3 ± 0.9 ng/mL and 22.5 ± 16.2 h·ng/mL, respectively. After daily application of ZILXI in subjects with inflammatory lesions of rosacea for 14 days, steady-state was reached by Day 1 and systemic accumulation of minocycline was not evident.

13 NONCLINICAL TOXICOLOGY

13.1 Carcinogenesis, Mutagenesis, Impairment of Fertility

In a carcinogenicity study in which minocycline hydrochloride was orally administered to male and female rats once daily for up to 104 weeks at dosages up to 200 mg/kg/day, minocycline hydrochloride was associated in both sexes with follicular cell tumors of the thyroid gland, including increased incidences of adenomas, carcinomas and the combined incidence of adenomas and carcinomas in males, and adenomas and the combined incidence of adenomas and carcinomas in females. In a carcinogenicity study in which minocycline hydrochloride was orally administered to male and female mice once daily for up to 104 weeks at dosages up to 150 mg/kg/day, exposure to minocycline hydrochloride did not result in a significantly increased incidence of neoplasms in either males or females.

Minocycline was not mutagenic in vitro in a bacterial reverse mutation assay (Ames test) or CHO/HGPRT mammalian cell assay in the presence or absence of metabolic activation. Minocycline was not clastogenic in vitro using human peripheral blood lymphocytes or in vivo in a mouse micronucleus test.

Male and female reproductive performance in rats was unaffected by oral doses of minocycline of up to 300 mg/kg/day (27,500 times the systemic exposure at the MRHD based on AUC comparison). However, oral administration of 100 or 300 mg/kg/day of minocycline to male rats (10,000 or 27,500 times, respectively, the systemic exposure at the MRHD based on AUC comparison), adversely affected spermatogenesis.

Effects observed at 300 mg/kg/day of oral minocycline included a reduced number of sperm cells per gram of epididymis, an apparent reduction in the percentage of sperm that were motile, and (at 100 and 300 mg/kg/day) increased numbers of morphologically abnormal sperm cells. Morphological abnormalities observed in sperm samples included absent heads, misshapen heads, and abnormal flagella.

14 CLINICAL STUDIES

The safety and efficacy of once daily use of ZILXI was assessed in two 12-week multicenter, randomized, double-blind, vehicle-controlled trials in subjects with inflammatory lesions of rosacea (Trial 1 [NCT02601963] and Trial 2 [NCT03142451]). Efficacy was assessed in a total of 1,522 subjects 18 years of age and older. ZILXI or its vehicle were applied once daily for 12 weeks; no other topical or systemic medication affecting the course of inflammatory lesions of rosacea was permitted for use during these trials.

Subjects were required to have an inflammatory lesion count in the range 15-75 lesions and an Investigator Global Assessment (IGA) score of 3 (“moderate”) or 4 (“severe”) at baseline.

Overall, 96% of subjects were White and 71% were female. Three hundred and eighty-three (25%) subjects were 18 to 40 years of age, 899 (59%) subjects were 41 to 64 years of age, and 240 (16%) subjects were 65 years or older. At baseline, subjects had a mean inflammatory lesion count of 29.4. Additionally, approximately 87% of subjects had an IGA score of 3 (“moderate”).

The co-primary efficacy endpoints were the absolute change from baseline in inflammatory lesion counts at Week 12 and the proportion of subjects with treatment success at Week 12, defined as an IGA score of 0 (“clear”) or 1 (“almost clear”), and at least a two-grade improvement (decrease) from baseline at Week 12. The efficacy results are presented in Table 2.

Table 2 Efficacy of ZILXI at Week 12
 | Trial 1 |  | Trial 2
 | ZILXI; (N=495) | Vehicle; (N=256) | ZILXI; (N=514) | Vehicle; (N=257)
IGA Success (1) | 52.1% | 43.0% | 49.1% | 39.0%
Treatment Difference (95% CI) (2) | 9.0%; (1.3%, 16.8%) |  | 10.2%; (3.1%, 17.4%)
Inflammatory Lesion Count
Mean Absolute Change from Baseline (3) | -17.6 | -15.4 | -18.4 | -14.5
Treatment Difference (95% CI) (4) | -2.2; (-3.7, -0.7) |  | -3.9; (-5.5, -2.2)
Mean Percent Change from Baseline (3) | -61.3% | -54.1% | -60.2% | -48.9%
Treatment Difference (95% CI) (4) | -7.3%; (-12.5%, -2.1%) |  | -11.3%; (-16.7%, -5.9%)
CI: Confidence Interval
(1) IGA Success is defined as an IGA score of 0 or 1 and at least a 2-grade improvement from baseline
(2) Treatment Difference and 95% CI are based on the CMH test stratified by analysis center
(3) Means presented in table are Least Square means
(4) Treatment Difference and 95% CI are based on ANCOVA model with treatment and analysis center as factors, and baseline value as covariate

16 HOW SUPPLIED/STORAGE AND HANDLING

How Supplied

ZILXI® (minocycline) topical foam, 1.5% is a yellow suspension supplied in a pressurized aluminum aerosol container (can). Each gram of ZILXI contains 15 mg of minocycline equivalent to 16 mg of minocycline hydrochloride, and is supplied as follows:

NDC 69489-212-30 30 g Can

Storage

ZILXI must be stored at 2 ºC – 8 ºC (36 ºF – 46 ºF) until dispensed to the patient.

Once dispensed, the patient is to store ZILXI at room temperature below 25 ºC (77 ºF) for 90 days. Do not store in the refrigerator.

Handling

Allow the can to warm to room temperature before first use.

Shake can well before use.

WARNING: Flammable. Avoid fire, flame, or smoking during and immediately following application. Contents under pressure. Do not puncture or incinerate. Do not expose to heat or temperatures above 49 oC (120 oF).

17 PATIENT COUNSELING INFORMATION

Advise the patient to read the FDA-approved patient labeling (Patient Information and Instructions for Use).

Inform patients using ZILXI (minocycline) topical foam, 1.5% of the following information and instructions:

Flammability

The propellant in ZILXI is flammable. Instruct the patient to avoid fire, flame, and smoking during and immediately following application.

Tooth Discoloration

Advise caregivers of pediatric patients that ZILXI may cause permanent discoloration of deciduous and permanent teeth during tooth development (generally up to the age of 8 years) based on observations with oral tetracycline.

Lactation

Advise women that breastfeeding is not recommended during ZILXI therapy.

Tissue Hyperpigmentation

Inform patients that ZILXI may cause discoloration of skin, scars, teeth or gums based on observations with oral minocycline.

Clostridioides difficile Associated Diarrhea

Advise patients that Clostridioides difficile associated diarrhea can occur with oral minocycline therapy. Advise patients to seek medical attention if they develop watery or bloody stools while using ZILXI.

Hepatotoxicity

Inform patients about the possibility of hepatotoxicity reported with oral minocycline. Advise patients to seek medical advice if they experience symptoms or signs of hepatotoxicity, including loss of appetite, tiredness, diarrhea, jaundice, increased bleeding tendencies, confusion, and sleepiness.

Central Nervous System Effects

Inform patients that central nervous system adverse reactions including dizziness or vertigo have been reported with oral minocycline therapy. Caution patients about driving vehicles or using hazardous machinery if they experience such symptoms while on ZILXI.

Intracranial Hypertension

Inform patients that intracranial hypertension can occur with minocycline therapy. Advise patients to seek medical attention if they develop unusual headache, visual symptoms, such as blurred vision, diplopia, and vision loss.

Photosensitivity

Inform patients that photosensitivity manifested by an exaggerated sunburn reaction has been observed in some individuals taking oral tetracyclines, including minocycline. Advise patients to minimize or avoid exposure to natural or artificial UV light (tanning beds or UVA/B treatment) while using ZILXI. Discuss other sun protection measures, if patients need to be outdoors while using ZILXI. Advise patients to discontinue treatment at the first evidence of sunburn.

Autoimmune Syndromes

Inform patients that autoimmune syndromes, including drug-induced lupus-like syndrome, autoimmune hepatitis, vasculitis and serum sickness have been observed with oral tetracycline-class drugs, including minocycline. Symptoms may be manifested by arthralgia, fever, rash and malaise. Advise patients who experience such symptoms to stop the drug immediately and seek medical help.

Other Information

ZILXI should be applied exactly as directed.
ZILXI may stain fabric.

Manufactured by: ASM Aerosol-Service AG, Mohlin, Switzerland
Manufactured for: Journey Medical Corporation, Scottsdale, AZ 85258
Product of Portugal or Italy

ZIL-P01-R01

ZILXI is a registered trademark of Journey Medical Corporation.
All other trademarks are the properties of their respective owners.
Copyright © 2023, Journey Medical Corporation. All rights reserved.

PATIENT INFORMATION

ZILXI® (ZILK-see)

(minocycline)

topical foam

Important Information: ZILXI is for use on the skin only (topical use). ZILXI is not for use in your mouth, eyes, or vagina.

What is ZILXI?

ZILXI is a prescription medicine used on the skin (topical) to treat adults with pimples and bumps caused by a condition called rosacea.

ZILXI should not be used for the treatment of infections.

It is not known if ZILXI is safe and effective in children.

Do not use ZILXI if you are allergic to any tetracycline medicines or to any of the ingredients in ZILXI. Ask your healthcare provider or pharmacist for a list of these medicines if you are not sure.

Before using ZILXI, tell your healthcare provider about all of your medical conditions, including if you:

- have diarrhea or watery stools
- have liver problems
- have kidney problems
- are pregnant or plan to become pregnant.Taking tetracycline medicines by mouth during pregnancy may cause serious side effects on the growth of bone and teeth of your baby. ZILXI topical foam is used on your skin and it is not known if it will harm your unborn baby.
- are breastfeeding or plan to breastfeed. Do not breastfeed during treatment with ZILXI.

Tell your healthcare provider about all the other medicines you take, including prescription and over-the-counter medicines, vitamins and herbal supplements, and skin products you use. Tetracycline medicines taken by mouth may affect the way other medicines work and may increase your chance of developing certain side effects.

Especially tell your healthcare provider if you take:

- a blood thinner medicine
- a penicillin antibiotic medicine
- isotretinoin

Ask your healthcare provider or pharmacist if you are not sure if your medicine is one that is listed above. Know the medicines you take. Keep a list of them to show your healthcare provider and pharmacist.

How should I use ZILXI?

- See the detailed “Instructions for Use” included with this leaflet for directions about how to apply ZILXI the right way.
- Use ZILXI exactly as your healthcare provider tells you.
- Apply ZILXI to your entire face at about the same time each day, at least 1 hour before bedtime. You should apply enough ZILXI to cover the entire face.
- Do not bathe, shower, or swim for at least 1 hour after applying ZILXI.
- Wash your hands after applying ZILXI.

What should I avoid while using ZILXI?

- ZILXI is flammable. Avoid fire, flames, and smoking when applying and right after you apply ZILXI.
- Limit your time in sunlight. Avoid sunlight or artificial sunlight such as sunlamps or tanning beds. Use sun protection measures such as sunscreen and wear loose-fitting clothes that cover your skin while out in sunlight. Stop using ZILXI if you get sunburn.
- Minocycline taken by mouth may cause feelings of light-headedness, dizziness, or spinning (vertigo). You should not drive or operate dangerous machinery if you have these symptoms during treatment with ZILXI.

What are possible side effects of ZILXI?

ZILXI contains minocycline, a tetracycline medicine. Tetracyclines, when taken by mouth, may cause serious side effects, including:

- Harm to an unborn baby. See “What should I tell my healthcare provider before using ZILXI?”
- Permanent tooth discoloration. Tetracycline medicine when taken by mouth may permanently turn a baby or child's teeth yellow-gray-brown during tooth development. You should not use ZILXI during tooth development. Tooth development happens in the second and third trimesters of pregnancy, and from birth up to 8 years of age.
- Slow bone growth. Tetracycline medicine taken by mouth may slow bone growth in infants and children. Slow bone growth is reversible after stopping treatment.
- Diarrhea. Diarrhea can happen with most antibiotics, including minocycline taken by mouth. This diarrhea may be caused by an infection (Clostridioides difficile) in your intestines. Call your healthcare provider right away if you get watery or bloody stools while using ZILXI.
- Liver problems. Minocycline taken by mouth can cause serious liver problems that may lead to death. Stop using ZILXI and call your healthcare provider right away if you get any of the following signs or symptoms of liver problems:

o loss of appetite

o tiredness

o diarrhea

o yellowing of your skin or the white of your eyes (jaundice)

o bleeding more easily than normal

o confusion

o sleepiness

- Central nervous system effects. See “What should I avoid while using ZILXI?”
- Increased pressure in the brain (intracranial hypertension). This condition may lead to vision changes and permanent vision loss. You are more likely to get intracranial hypertension if you are a female of childbearing potential and are overweight or have a history of intracranial hypertension. Stop using ZILXI and tell your healthcare provider right away if you have blurred vision, double vision, vision loss, or unusual headaches.
- Immune system reactions including a lupus-like syndrome, hepatitis, and inflammation of blood or lymph vessels (vasculitis) have happened during treatment with minocycline taken by mouth. Call your healthcare provider right away if you get a fever, rash, joint pain, or body weakness.
- Sensitivity to sunlight (photosensitivity). See “What should I avoid while using ZILXI?”
- Serious skin or allergic reactions have happened during treatment with minocycline taken by mouth that may affect parts of your body such as your liver, lungs, kidneys and heart. Sometimes these can lead to death. Stop using ZILXI and go to the nearest hospital emergency room right away if you have any of the following signs or symptoms:

o skin rash, hives, sores in your mouth, or your skin blisters and peels

o swelling of your face, eyes, lips, tongue, or throat

o trouble swallowing or breathing

o blood in your urine

o fever, yellowing of the skin or the whites of your eyes (jaundice), dark colored urine

o pain on the right side of the stomach area (abdominal pain)

o chest pain or abnormal heartbeats

o swelling in your legs, ankles, and feet

•Discoloration (hyperpigmentation). Minocycline taken by mouth may cause darkening of your skin, scars, teeth, or gums.

The most common side effect of ZILXI is diarrhea.

Your healthcare provider may stop your treatment with ZILXI if you develop certain side effects.

These are not all the possible side effects with ZILXI.

Call your doctor for medical advice about side effects. You may report side effects to FDA at 1-800-FDA-1088.

How should I store ZILXI?

- Store ZILXI at room temperature below 77ºF (25ºC) for 90 days.
- Do not store ZILXI in the refrigerator.
- Do not puncture or burn the ZILXI can.
- Do not expose to heat or temperatures above 120ºF (49ºC)

Keep ZILXI and all medicines out of the reach of children.

General information about the safe and effective use of ZILXI.

Medicines are sometimes prescribed for purposes other than those listed in Patient Information leaflet. Do not use ZILXI for a condition for which it was not prescribed. Do not give ZILXI to other people, even if they have the same symptoms you have. It may harm them. You can also ask your healthcare provider or pharmacist for information about ZILXI that is written for health professionals.

What are the ingredients in ZILXI?

Active ingredient: minocycline

Inactive ingredients: soybean oil, coconut oil, light mineral oil, cyclomethicone, cetostearyl alcohol, stearic acid, myristyl alcohol, hydrogenated castor oil, white wax (beeswax), stearyl alcohol, docosanol. ZILXI is dispensed from an aluminum container (can) pressurized with propellant (butane + isobutane + propane).
Manufactured by: ASM Aerosol-Service AG, Mohlin, Switzerland

Manufactured for: Journey Medical Corporation, Scottsdale, AZ 85258

Product of Portugal or Italy

ZIL-P02-R01

ZILXI is a registered trademark of Journey Medical Corporation.

All other trademarks are the properties of their respective owners.

Copyright © 2023, Journey Medical Corporation. All rights reserved.

For more information, go to www.ZILXI.com or call Journey Medical Corporation at 1-855-531-1859.

This Patient Information has been approved by the U.S. Food and Drug Administration Issued: 07/2023

Instructions for Use
ZILXI® (ZILK-see)
(minocycline)
topical foam

Important Information: ZILXI is for use on skin only (topical use). ZILXI is not for use in your mouth, eyes or vagina.

Read this Instructions for Use before you start using ZILXI and each time you get a refill. There may be new information. This information does not take the place of talking with your healthcare provider about your medical condition or treatment. Use ZILXI exactly as your healthcare provider tells you.

Before applying ZILXI:

- When using a new ZILXI can, wait until the can has warmed to room temperature before use.
- If necessary, wash your face gently with a mild non-medicated cleanser, rinse with water, and pat your skin dry.
- Apply ZILXI to your entire face at about the same time each day, at least 1 hour before bedtime.

Step 1: Shake the can well. Place thumb under tab above nozzle and lift up to remove the cap from the ZILXI can.

Step 2: Press the top of the can to dispense a small amount (cherry-sized amount) of ZILXI onto your fingertips.

Step 3: Apply a thin layer of ZILXI and gently rub onto your entire face. You may need to use additional ZILXI to make sure that your entire face is treated.

- Wash your hands after applying ZILXI.
- ZILXI can stain fabric.

This Instructions for Use has been approved by the U.S. Food and Drug Administration. Issued: 07/2023

Manufactured by:
ASM Aerosol-Service AG, Mohlin, Switzerland
Manufactured for:
Journey Medical Corporation, Scottsdale, AZ 85258

Product of Portugal or Italy

ZIL-P03-R01

ZILXI is a registered trademark of Journey Medical Corporation.
All other trademarks are the properties of their respective owners.
Copyright © 2023, Journey Medical Corporation. All rights reserved.

PACKAGE LABEL

Container Label (NDC 69489-212-07) - ZILXI 7 gram Physician Sample

NDC 69489-212-07

Physician Sample

Not for Sale

zilxi®

(minocycline)
topical foam, 1.5%

For topical use only, not for oral,

ophthalmic or intravaginal use

Rx only 7g

Carton (NDC 69489-212-07) - ZILXI 7 gram Physician Sample

NDC 69489-212-07 Physician Sample

Not for Sale

zilxi®

(minocycline)
topical foam, 1.5%

For topical use only,

not for oral, ophthalmic

or intravaginal use

Rx only

7 g JOURNEY

PACKAGE LABEL

Container Label (NDC 69489-212-30) - ZILXI 30 gram Trade Package

NDC 69489-212-30

zilxi®

(minocycline)
topical foam, 1.5%

For topical use only,

not for oral, ophthalmic

or intravaginal use

Rx only 30 g

Carton (NDC 69489-212-30) - ZILXI 30 gram Trade Package

NDC 69489-212-30

zilxi®

(minocycline)
topical foam, 1.5%

For topical use only,

not for oral, ophthalmic

or intravaginal use

Rx only

30g JOURNEY

PACKAGE LABEL

Container Label (NDC 69489-212-03) - ZILXI 3 gram Physician Sample

NDC 69489-212-03 Physician Sample

Not for Sale

zilxi®

(minocycline)
topical foam, 1.5%

For topical use only, not for oral,

ophthalmic or intravaginal use

Rx only 3 g

Carton (NDC 69489-212-03) - ZILXI 3 gram Physician Sample

NDC 69489-212-03 Physician Sample

Not for Sale

zilxi®

(minocycline)
topical foam, 1.5%

For topical use only, not for oral,

ophthalmic or intravaginal use

Rx only

3 g JOURNEY